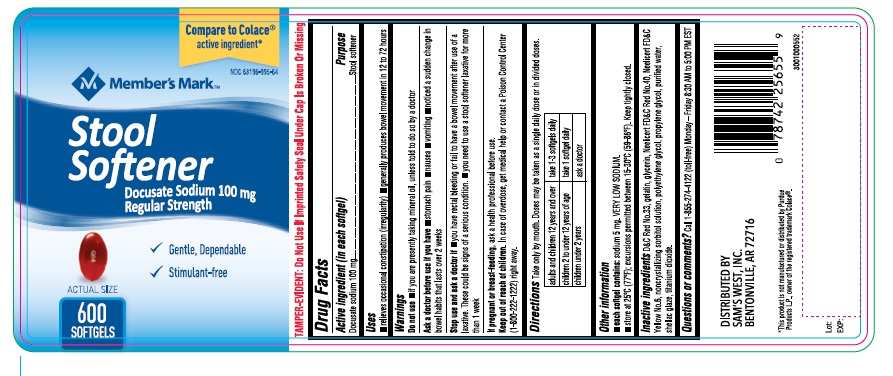 DRUG LABEL: DOCUSATE SODIUM
NDC: 68196-995 | Form: CAPSULE
Manufacturer: Sam's West Inc
Category: otc | Type: Human OTC Drug Label
Date: 20241024

ACTIVE INGREDIENTS: DOCUSATE SODIUM 100 mg/1 1
INACTIVE INGREDIENTS: D&C RED NO. 33; GELATIN TYPE B BOVINE (160 BLOOM); GLYCERIN; FD&C RED NO. 40; FD&C YELLOW NO. 6; SORBITOL; POLYETHYLENE GLYCOL 400; PROPYLENE GLYCOL; WATER; SHELLAC; TITANIUM DIOXIDE

Drug Facts

Active ingredient

(in each softgel)
Docusate sodium 100 mg

Purpose

Stool softener

Uses

- relieves occasional constipation (irregularity)
- generally produces bowel movement in 12 to 72 hours

Warnings

Do not use

- if you are presently taking mineral oil, unless told to do so by a doctor

Ask a doctor before use if you have

- stomach pain
- nausea
- vomiting
- noticed a sudden change in bowel habits that lasts over 2 weeks

Stop use and ask a doctor if

- you have rectal bleeding or fail to have a bowel movement after use of a laxative. These could be signs of a serious condition.
- you need to use a stool softener laxative for more than 1 week

If pregnant or breast-feeding,

ask a health professional before use.

Keep out of reach of children.

In case of overdose, get medical help or contact a Poison Control Center (1-800-222-1222) right away.

Directions

Take only by mouth. Doses may be taken as a single daily dose or in divided doses.

adults and children 12 years and over | take 1-3 softgel daily
children 2 to under 12 years of age | take 1 softgel daily
children under 2 years | ask a doctor

Other information

- each capsule contains: sodium 5 mg Very Low Sodium
- store at 25°C (77°F); excursions permitted between 15-30ºC (59-86ºF). Keep tightly closed.

Inactive ingredients

D&C Red No.33, gelatin, glycerin, Neelicert FD&C Red No.40, Neelicert FD&C Yellow No.6, noncrystallizing sorbitol solution, polyethylene glycol, propylene glycol, purified water, shellac glaze, titanium dioxide.

Questions or Comments?

Call 1-855-274-4122 (toll-free)

(Monday - Friday 8:30 AM to 5:00 PM EST)

*This product is not manufactured or distributed by Purdue Products L.P., owner of the registered trademark Colace®.

DISTRIBUTED BY
SAM'S WEST, INC.
BENTONVILLE, AR 72716

PACKAGE LABEL-PRINCIPAL DISPLAY PANEL - 100 mg (600 Capsules Container Label)

Compare to Colace®
active ingredient*

NDC 68196-995-64

Member's Mark™
Stool
Softener

Docusate sodium 100 mg

Regular Strength

- Gentle, Dependable
- Stimulant-free

600 Softgels